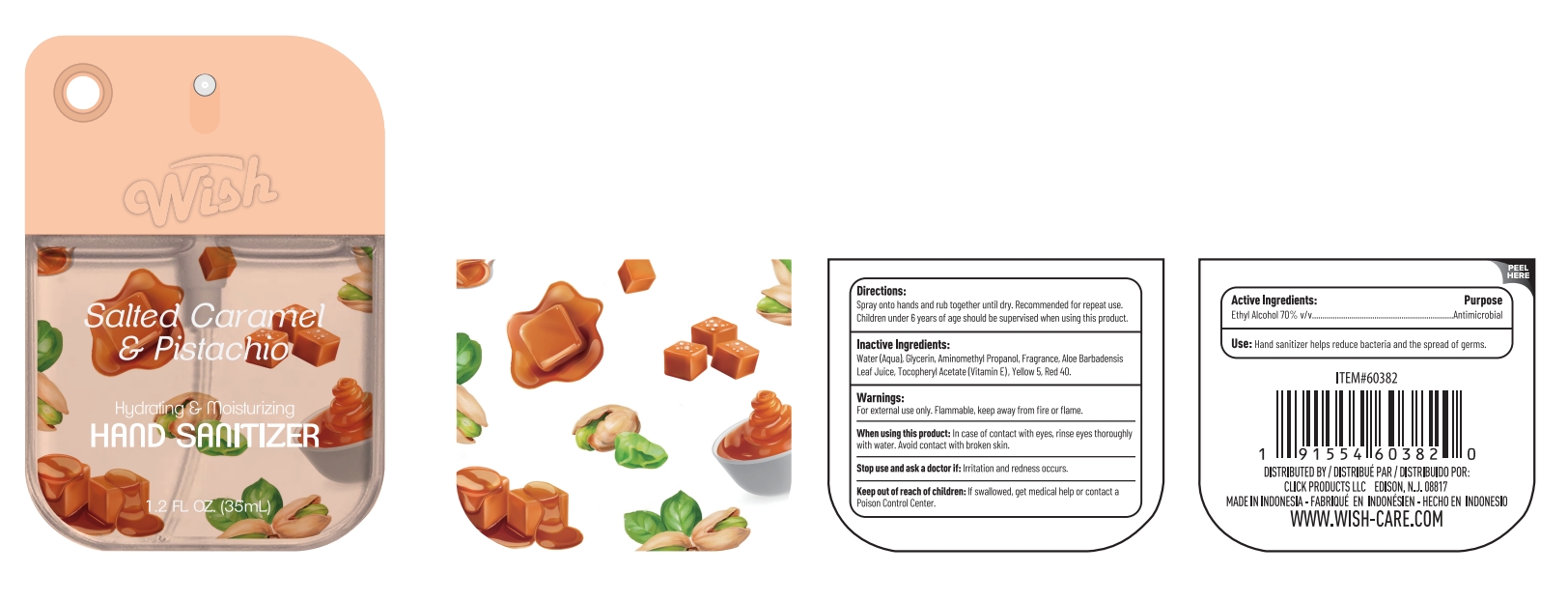 DRUG LABEL: WISH HAND SANITIZER SALTED CARAMEL PISTACHIO
NDC: 85537-110 | Form: SPRAY
Manufacturer: PT SUPER HOME PRODUCT INDONESIA
Category: otc | Type: HUMAN OTC DRUG LABEL
Date: 20250424

ACTIVE INGREDIENTS: ALCOHOL 70 mL/100 mL
INACTIVE INGREDIENTS: AQUA 25.9 mL/100 mL; PISTACHIO 2 mL/100 mL; GLYCERIN 2 mL/100 mL; ALOE BARBADENSIS LEAF JUICE 0.093 mL/100 mL; FD&C RED NO. 40 0.0005 mL/100 mL; FD&C YELLOW NO. 5 0.0005 mL/100 mL; .ALPHA.-TOCOPHEROL ACETATE 0.001 mL/100 mL; AMINOMETHYLPROPANOL 0.005 mL/100 mL

WISH HAND SANITIZER SALTED CARAMEL PISTACHIO

Directions:

Spray onto hands and rub together until dry. Recommended for repeat use.Children under 6 years of age should be supervised when using this product.

Inactive Ingredients:

Water(Aqua), Glycerin,Aminomethyl Propanol,Fragrance,Aloe Barbadensis Leaf Juice,Tocopheryl Acetate(Vitamin E),Yellow 5,Red 40.

Warnings:

For external use only. Flammable, keep away from fire or flame.

When using this product:

In case of contact with eyes, rinse eyes thoroughly with water. Avoid contact with broken skin.

Stop use and ask a doctor if:

Irritation and redness occurs.

Keep out of reach of children:

If swallowed, get medical help or contact a Poison Control Center.

Active Ingredients:

Ethyl Alcohol 70% v/v Purpose: Antimicrobial

Use:

Hand sanitizer helps reduce bacteria and the spread of germs.